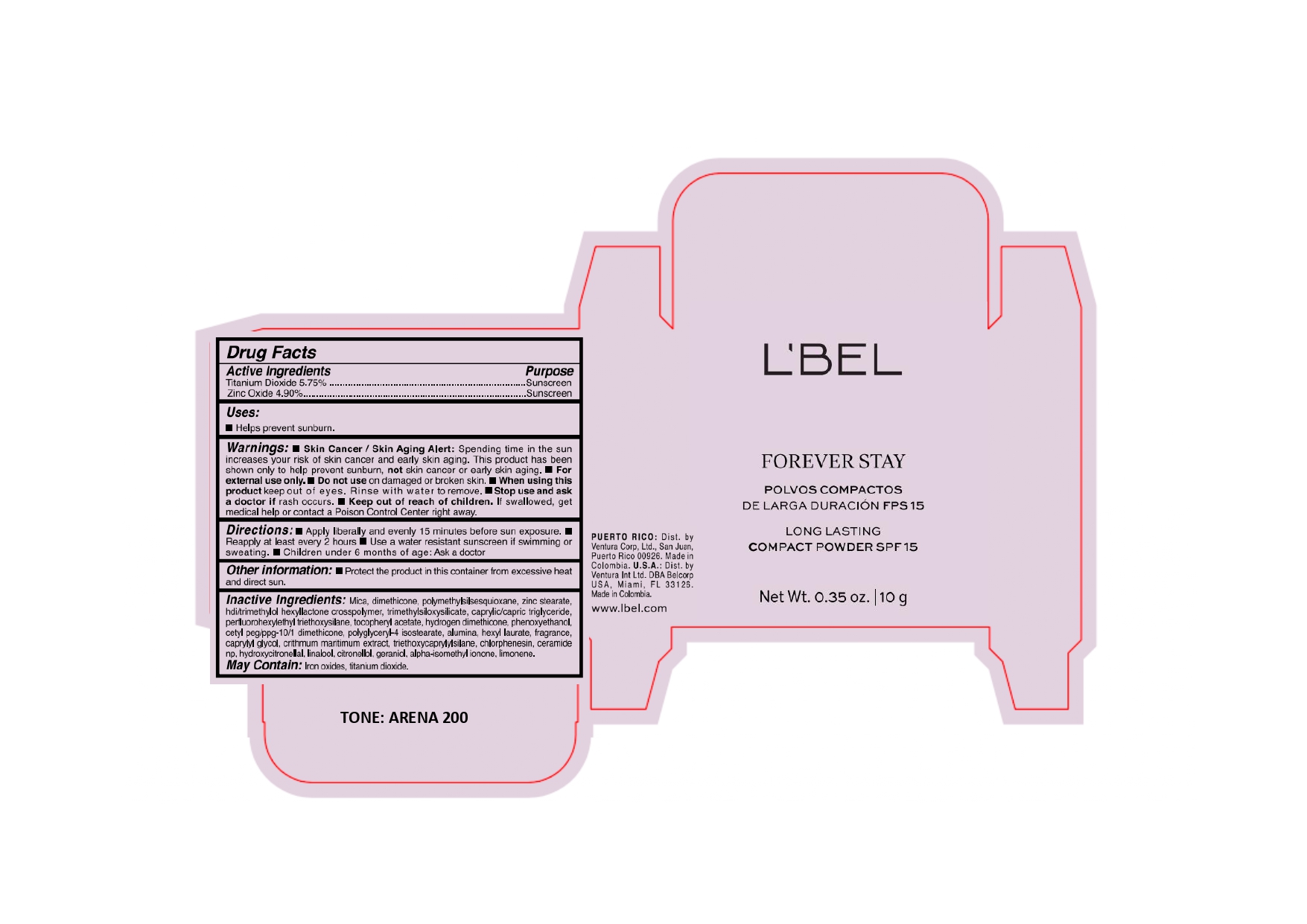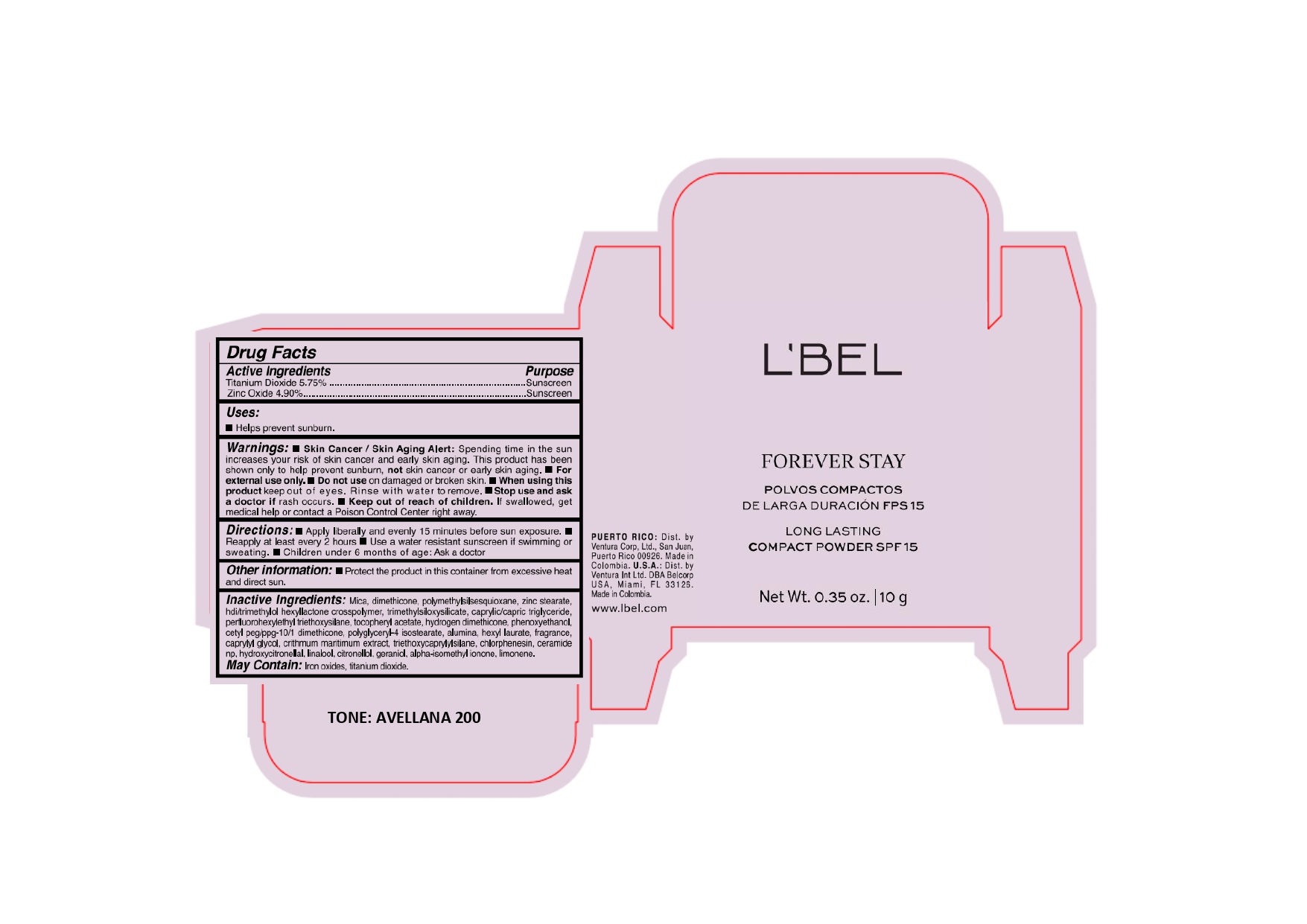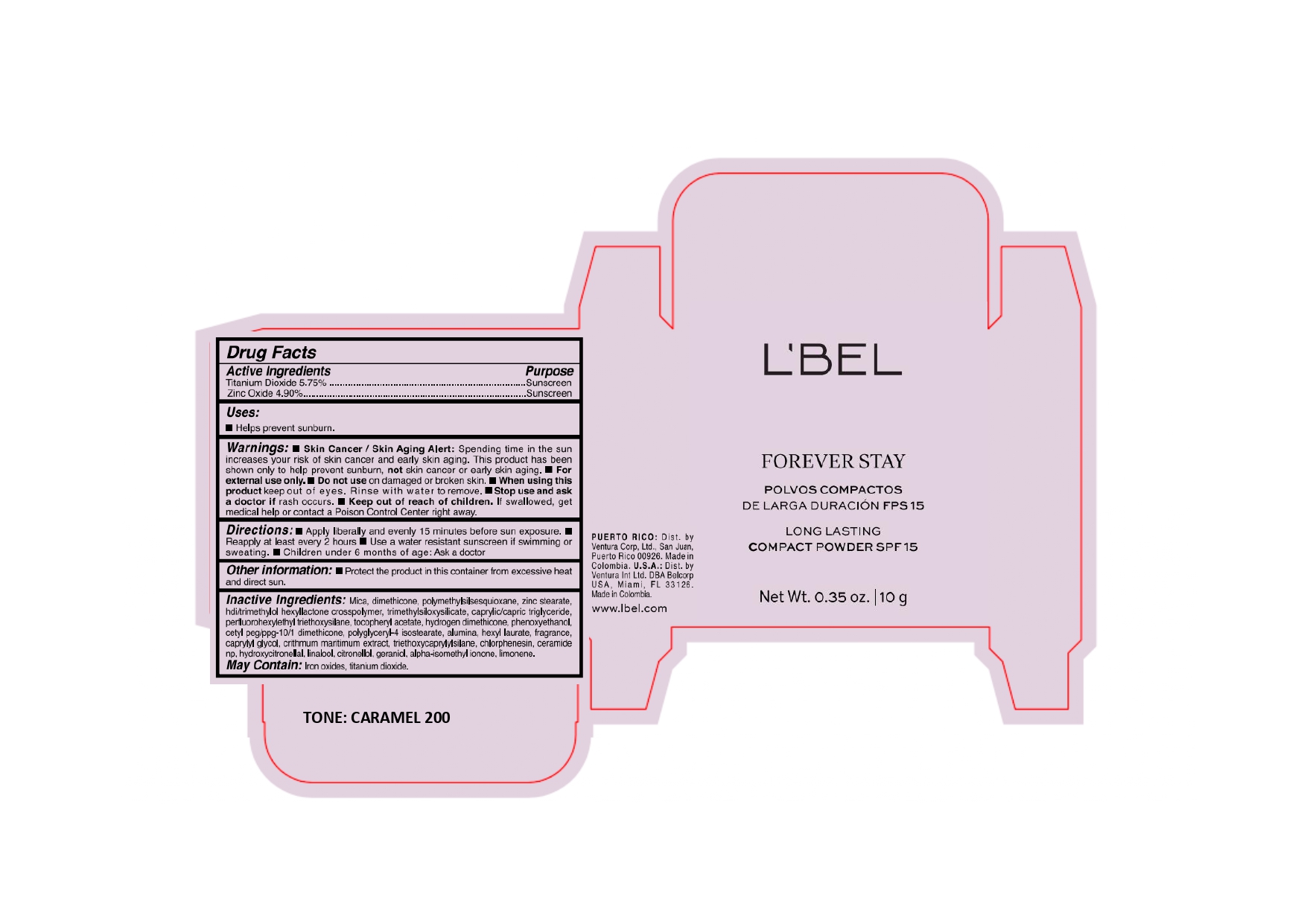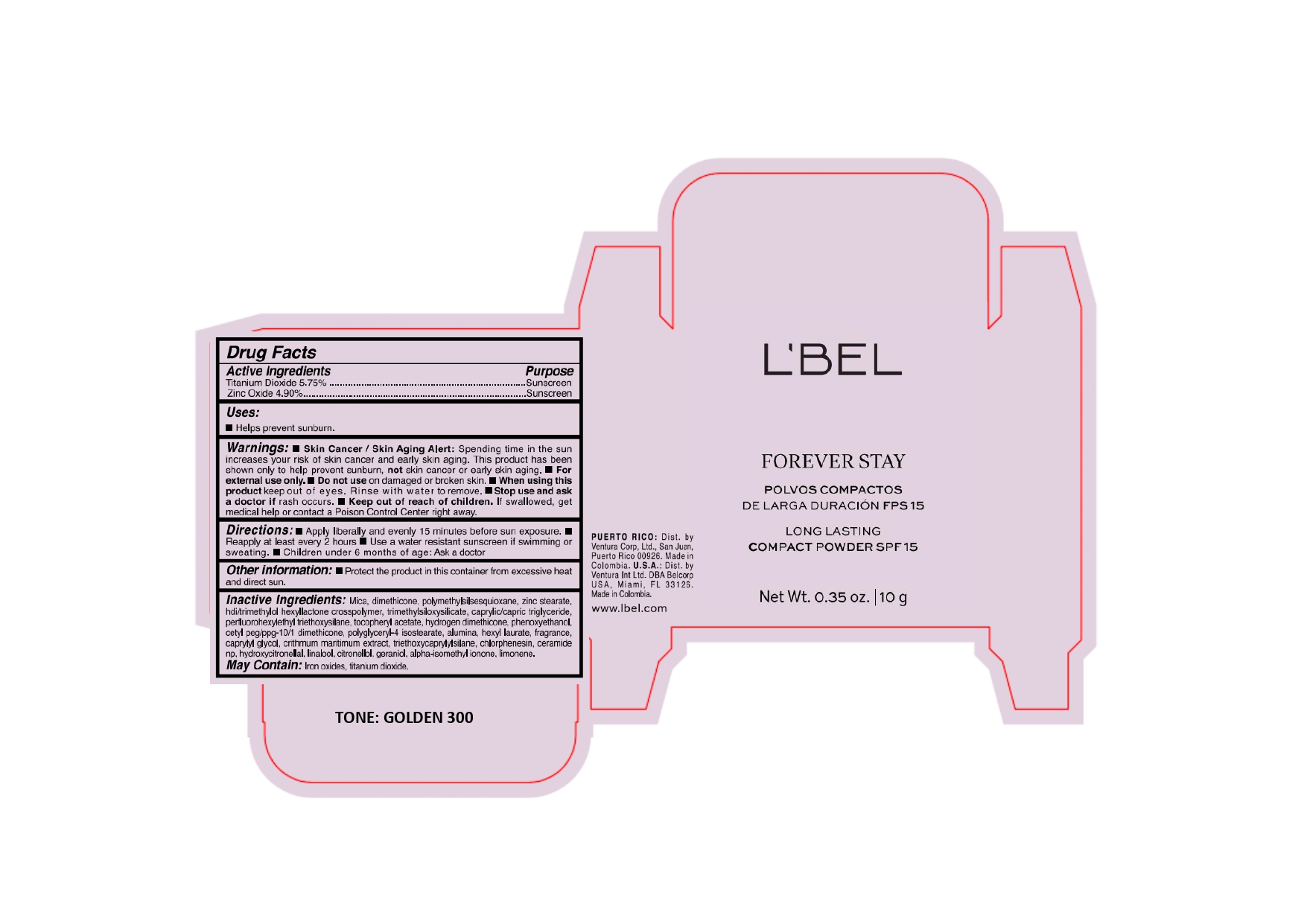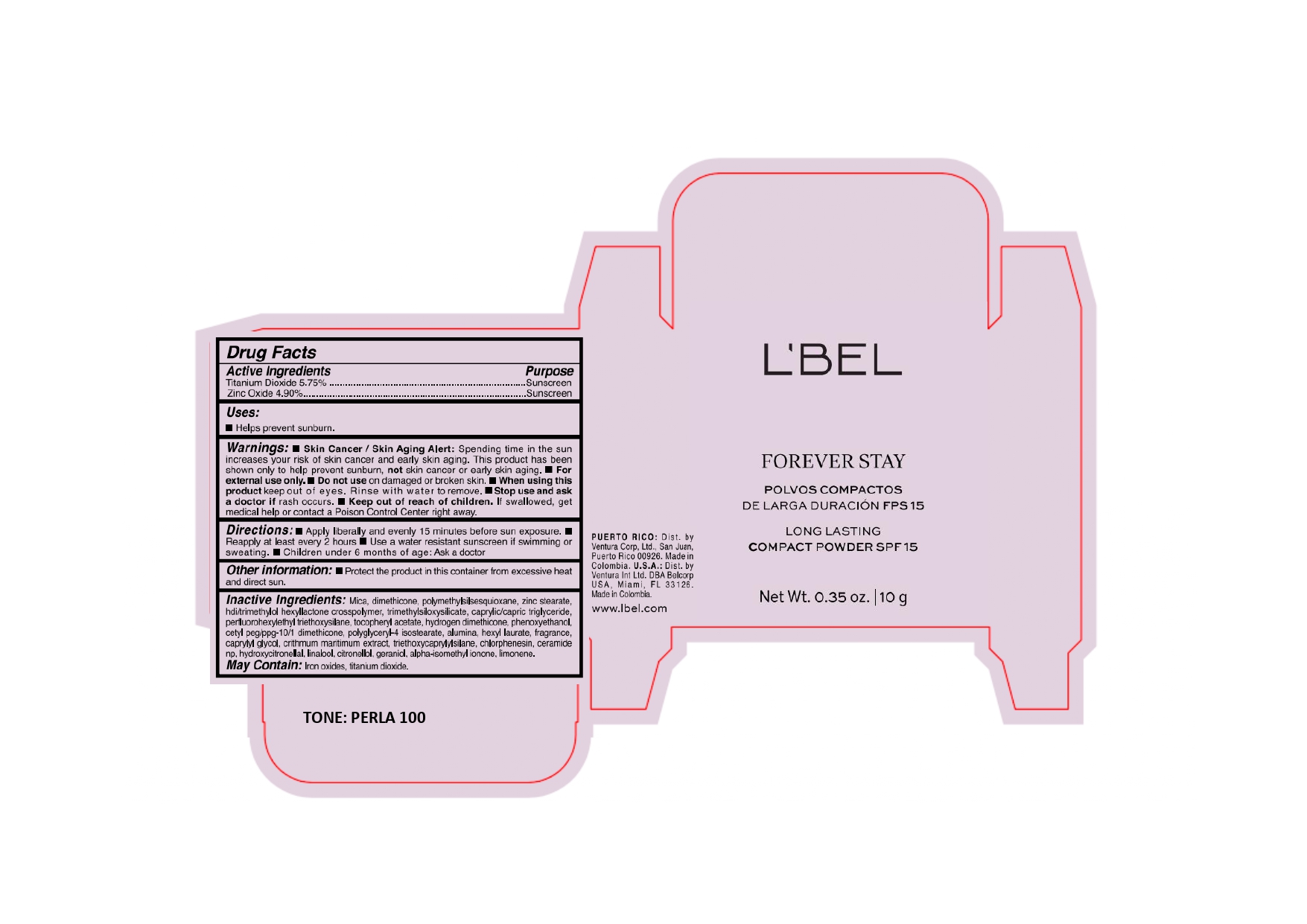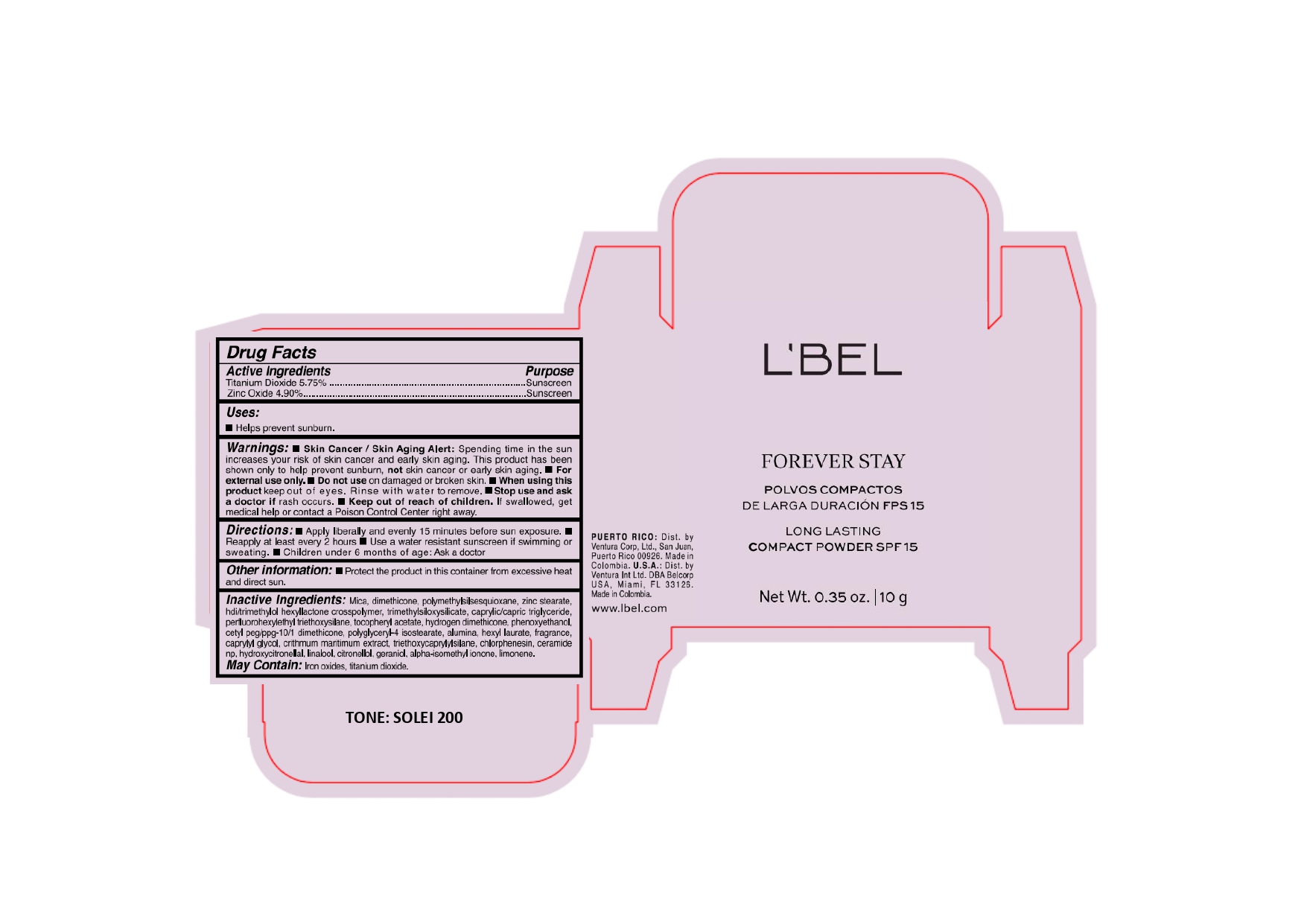 DRUG LABEL: LBEL FOREVER STAY POLVOS COMPACTOS DE LARGA DURACION FPS 15 LONG LASTING COMPACT SPF 15 PERLA 100
NDC: 14141-300 | Form: POWDER
Manufacturer: BEL STAR S A
Category: otc | Type: HUMAN OTC DRUG LABEL
Date: 20241204

ACTIVE INGREDIENTS: ZINC OXIDE 49 mg/1 g; TITANIUM DIOXIDE 57.5 mg/1 g
INACTIVE INGREDIENTS: MEDIUM-CHAIN TRIGLYCERIDES; PERFLUOROOCTYL TRIETHOXYSILANE; TRIMETHYLSILOXYSILICATE (M/Q 0.8-1.0); .BETA.-CITRONELLOL, (R)-; FERROSOFERRIC OXIDE; CETYL PEG/PPG-10/1 DIMETHICONE (HLB 5); CHLORPHENESIN; TRIETHOXYCAPRYLYLSILANE; HEXAMETHYLENE DIISOCYANATE/TRIMETHYLOL HEXYLLACTONE CROSSPOLYMER; MICA; HYDROXYCITRONELLAL; GERANIOL; ISOMETHYL-.ALPHA.-IONONE; HYDROGEN DIMETHICONE (13 CST); CRITHMUM MARITIMUM WHOLE; CERAMIDE NP; DIMETHICONE; ALUMINUM OXIDE; HEXYL LAURATE; FERRIC OXIDE YELLOW; PHENOXYETHANOL; POLYMETHYLSILSESQUIOXANE (4.5 MICRONS); POLYGLYCERYL-4 ISOSTEARATE; CAPRYLYL GLYCOL; .ALPHA.-TOCOPHEROL ACETATE; LINALOOL, (+/-)-; LIMONENE, (+/-)-; FERRIC OXIDE RED; ZINC STEARATE

L’BEL FOREVER STAY POLVOS COMPACTOS DE LARGA DURACIÓN FPS 15 LONG LASTING COMPACT POWDER SPF 15

Active Ingredients

Titanium Dioxide 5.75%

Zinc Oxide 4.90%

Purpose

Sunscreen

Uses

- Helps prevent sunburn.

Warnings

- Skin Cancer/Skin Aging Alert: Spending time in the sun increases your risk of skin cancer and early skin aging. This product has been shown only to help prevent sunburn, not skin cancer or early skin aging.
- For external use only.

Do not use

on damaged or broken skin.

When using this product

keep out of eyes. Rinse with water to remove.

Stop use and ask a doctor if

rash occurs.

Keep out of reach of children.

If swallowed, get medical help or contact a Poison Control Center right away.

Directions

- Apply liberally and evenly 15 minutes before sun exposure.
- Reapply at least every 2 hours.
- Use a water resistant sunscreen if swimming or sweating.
- Children under 6 months of age: Ask a doctor.

Other information

- Protect the product in this container from excessive heat and direct sun.

Inactive Ingredients:

Mica, dimethicone, polymethylsilsesquioxane, zinc stearate, hdi/trimethylol hexyllactone crosspolymer, trimethylsiloxysilicate, caprylic/capric triglyceride, perfluorohexylethyl triethoxysilane, tocopheryl acetate, hydrogen dimethicone, phenoxyethanol, cetyl peg/ppg-10/1 dimethicone, polyglyceryl-4 isostearate, alumina, hexyl laurate, fragrance, caprylyl glycol, crithmum maritimum extract, triethoxycaprylylsilane, chlorphenesin, ceramide np, hydroxycitronellal, linalool, citronellol, geraniol, alpha-isomethyl ionone, limonene.

May Contain: Iron oxides, titanium dioxide.

Company Information

PUERTO RICO: Dist. by Ventura Corp, Ltd., San Juan, Puerto Rico 00926.

Made in Colombia.

U.S.A.: Dist. by Ventura Int Ltd. DBA Belcorp USA, Miami, FL 33126.

Made in Colombia.

www.lbel.com